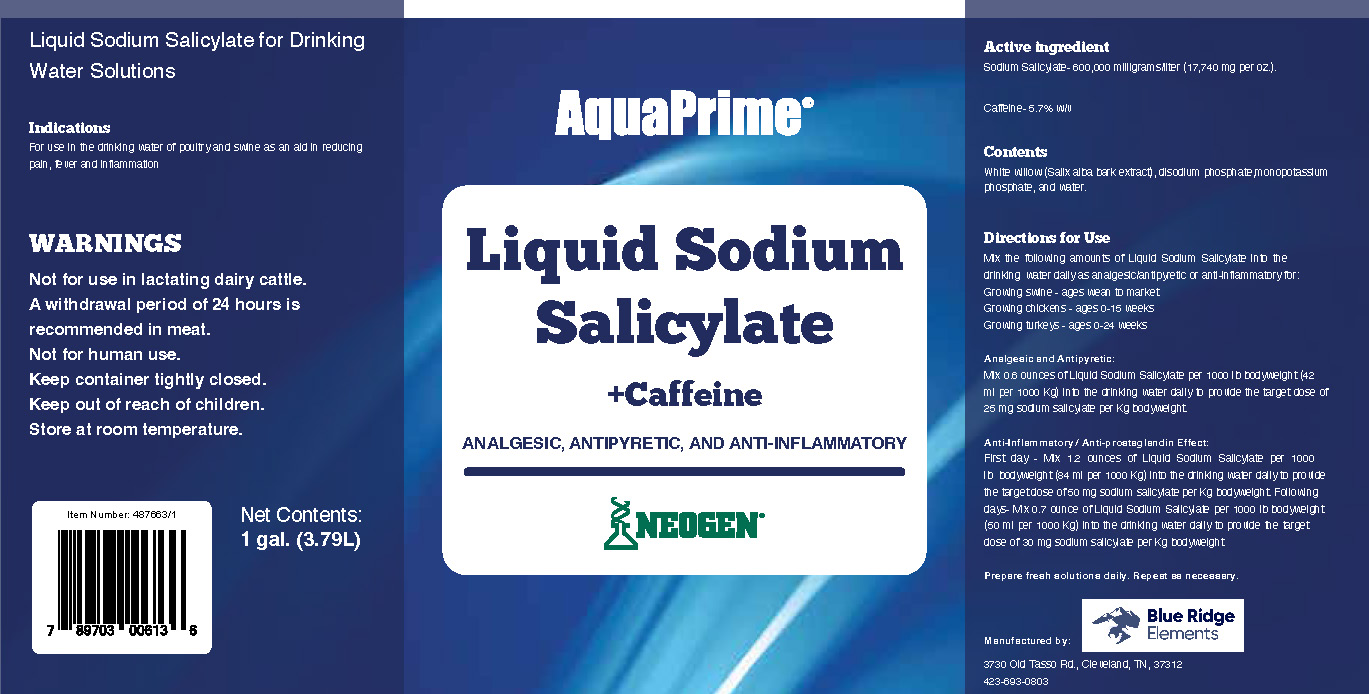 DRUG LABEL: AquaPrime Liquid Sodium Salicylate with Caffeine
NDC: 86050-3600 | Form: LIQUID
Manufacturer: Blendpack, Inc.
Category: animal | Type: OTC ANIMAL DRUG LABEL
Date: 20230725

ACTIVE INGREDIENTS: SODIUM SALICYLATE 600 g/1 L; CAFFEINE 57 g/1 L

AquaPrime Liquid Sodium Salicylate with Caffeine

Indications

For use in the drinking water of poultry and swine as an aid in reducing pain, fever and inflammation

Warnings

Not for use in lactating dairy cattle.

A withdrawal period of 24 hours is recommended in meat.

Not for human use.

Keep container tightly closed.

Keep out of reach of children.

Store at room temperature.

Directions for Use

Mix the following amounts of Liquid Sodium Salicylate into the drinking water daily as analgesic/antipyretic or anti-inflammatory for:
Growing swine - ages wean to market
Growing chickens - ages 0-15 weeks
Growing turkeys - ages 0-24 weeks

Analgesic and Antipyretic:

Mix 0.6 ounces of Liquid Sodium Salicylate per 1000 lb bodyweight (42 ml per 1000 Kg) into the drinking water daily to provide the target dose of 25 mg sodium salicylate per Kg bodyweight.

Anti-Inflammatory / Anti-prostaglandin Effect:

First day - Mix 1.2 ounces of Liquid Sodium Salicylate per 1000 lb bodyweight (84 ml per 1000 Kg) into the drinking water daily to provide the target dose of 50 mg sodium salicylate per Kg bodyweight.

Following days - Mix 0.7 ounce of Liquid Sodium Salicylate per 1000 lb bodyweight (50 ml per 1000 Kg) into the drinking water daily to provide the target dose of 30 mg sodium salicylate per Kg bodyweight.

Prepare fresh solutions daily. Repeat as necessary.

PACKAGE LABEL

Add image transcription here...